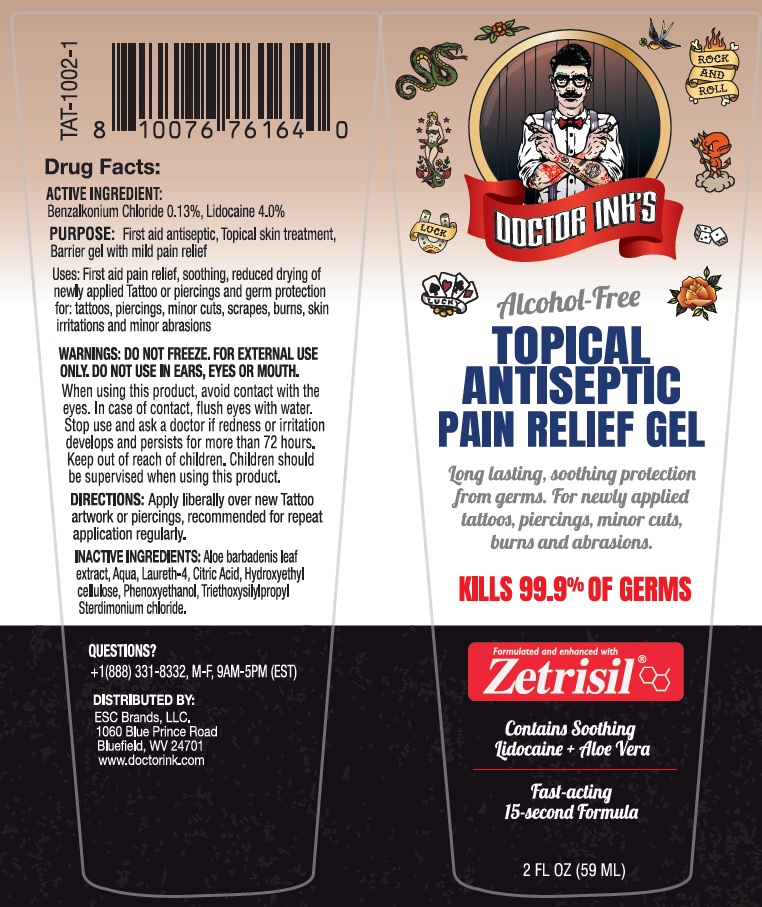 DRUG LABEL: DOCTOR INK TOPICAL ANTISEPTIC WITH PAIN RELIEF
NDC: 71884-204 | Form: GEL
Manufacturer: Enviro Specialty Chemicals Inc
Category: otc | Type: HUMAN OTC DRUG LABEL
Date: 20241231

ACTIVE INGREDIENTS: BENZALKONIUM CHLORIDE 1.3 mg/1 mL; LIDOCAINE 40 mg/1 mL
INACTIVE INGREDIENTS: ALOE VERA LEAF; WATER; LAURETH-4; CITRIC ACID MONOHYDRATE; HYDROXYETHYL CELLULOSE, UNSPECIFIED; PHENOXYETHANOL; TRIETHOXYSILYLPROPYL STEARDIMONIUM CHLORIDE

DOCTOR INK'S TOPICAL ANTISEPTIC PAIN RELIEF GEL

ACTIVE INGREDIENT:

Benzalkonium Chloride 0.13%, Lidocaine 4.0%

PURPOSE:

First aid antiseptic, Topical skin treatment, Barrier gel with mild pain relief

Uses:

First aid pain relief, soothing, reduced drying of newly applied Tattoo or piercings and germ protection for: tattoos, piercings, minor cuts, scrapes, burns, skin irritations and minor abrasions

WARNINGS:

DO NOT FREEZE. FOR EXTERNAL USE ONLY. DO NOT USE IN EARS, EYES OR MOUTH.

When using this product, avoid contact with the eyes. In case of contact, flush eyes with water. Stop use and ask a doctor if redness or irritation develops and persists for more than 72 hours.

Keep out of reach of children. Children should be supervised when using this product.

DIRECTIONS:

Apply liberally over new Tattoo artwork or piercings, recommended for repeat application regularly.

INACTIVE INGREDIENTS:

Aloe barbadensis leaf extract, Aqua, Laureth-4, Citric Acid, Hydroxyethyl cellulose, Phenoxyethanol, Triethoxysilylpropyl Steardimonium chloride.

QUESTIONS?

+1(888) 331-8332, M-F, 9AM-5PM (EST)

Alcohol-Free

Long lasting, soothing protection from germs.

KILLS 99.9% OF GERMS

Formulated and enhanced with Zetrisil®

Contains Soothing Lidocaine + Aloe Vera

Fast-acting
15-second Formula

DISTRIBUTED BY:
ESC Brands, LLC.
1060 Blue Prince Road
Bluefield, WV 24701
www.doctorink.com